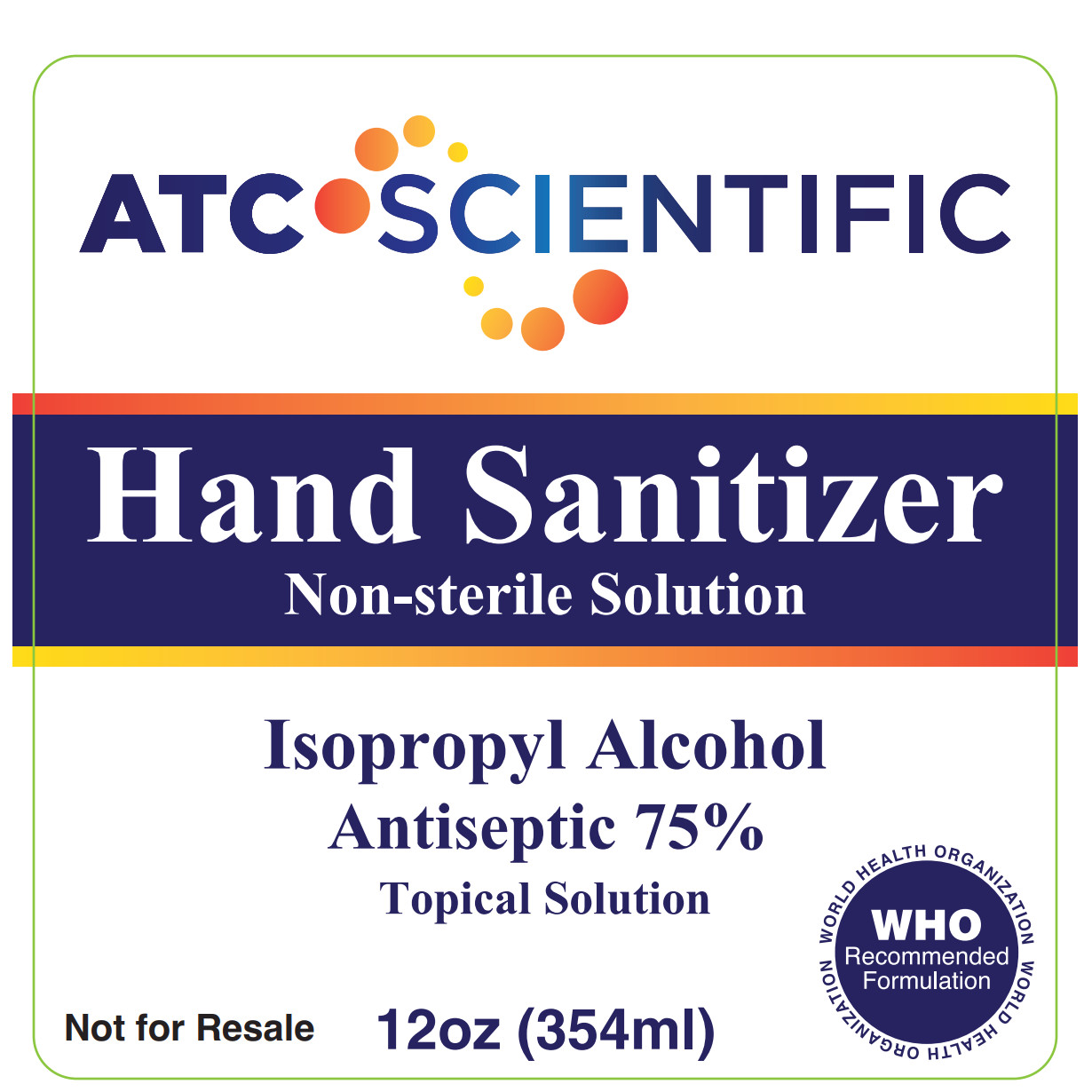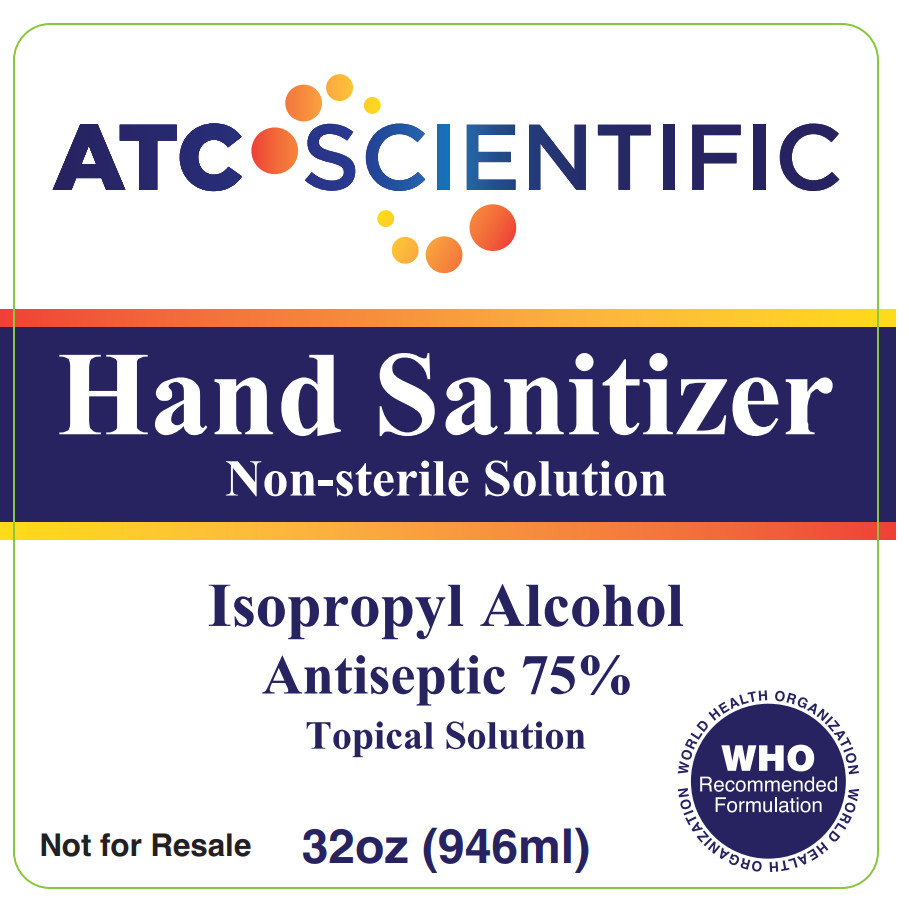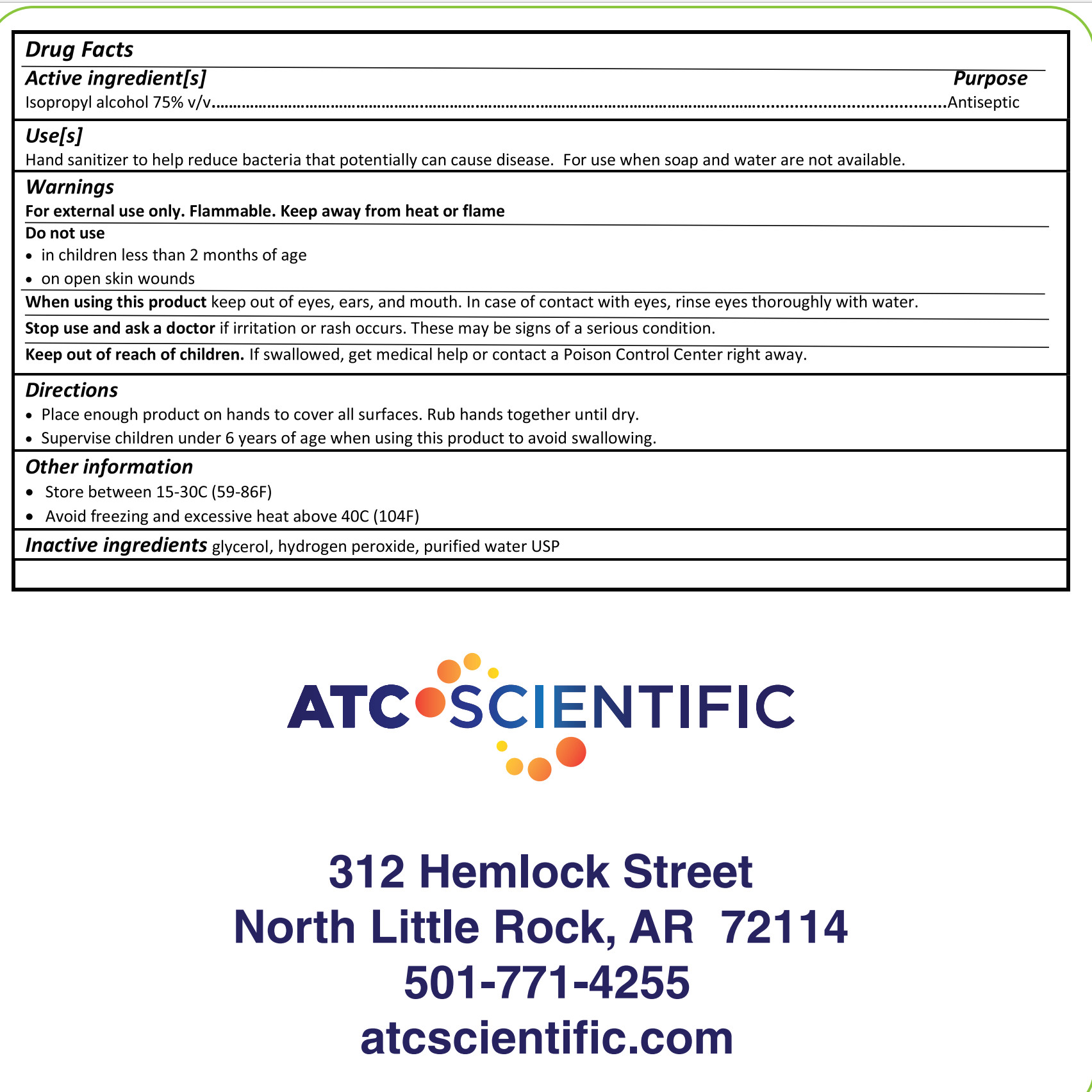 DRUG LABEL: Hand Sanitizer
NDC: 74133-101 | Form: LIQUID
Manufacturer: Atc Scientific, LLC
Category: otc | Type: HUMAN OTC DRUG LABEL
Date: 20200327

ACTIVE INGREDIENTS: ALCOHOL 75 mL/100 mL
INACTIVE INGREDIENTS: GLYCEROL FORMAL 1.45 mL/100 mL; HYDROGEN PEROXIDE 0.12 mL/100 mL

ATC Scientific Hand Sanitizer

Hand Sanitizer - 12oz & 32oz

Front Label - 12oz:

Front Label - 32oz:

Back Label (all sizes):

Purpose

Antiseptic

Warnings

Keep out of reach of children. If swallowed, get medical help or contact a Poison Control Center right away.

Warnings

For external use only. Keep away from heat or flame

Do not use in children less than 2 months of age

Do not use op open skin wounds

When using this product keep out of eyes, ears, and mouth. In case of contact with eyes, rinse eyes thoroughly with water.

Stop use and ask a doctor if irritation or rash occurs. These may be signs of a serious condition.

Keep out of reach of children. If swallowed, get medical help or contact a Poison Control Center right away.

Use(s)

Hand sanitizer to help reduce bacteria that potentially can cause disease. For use when soap and water are not available.

Inactive Ingredients

glycerol, hydrogen peroxide, purified water USP

Directions & Other Information

Place enough product on hands to cover all surfaces. Rub hands together until dry.

Supervise children under 6 years of age when using this product to avoid swallowing.

Store between 15-30C (59-86F)

Avoid freezing and excessive heat above 40C (104F)

Active Ingredient(s)

Isopropyl alcohol 75% v/v